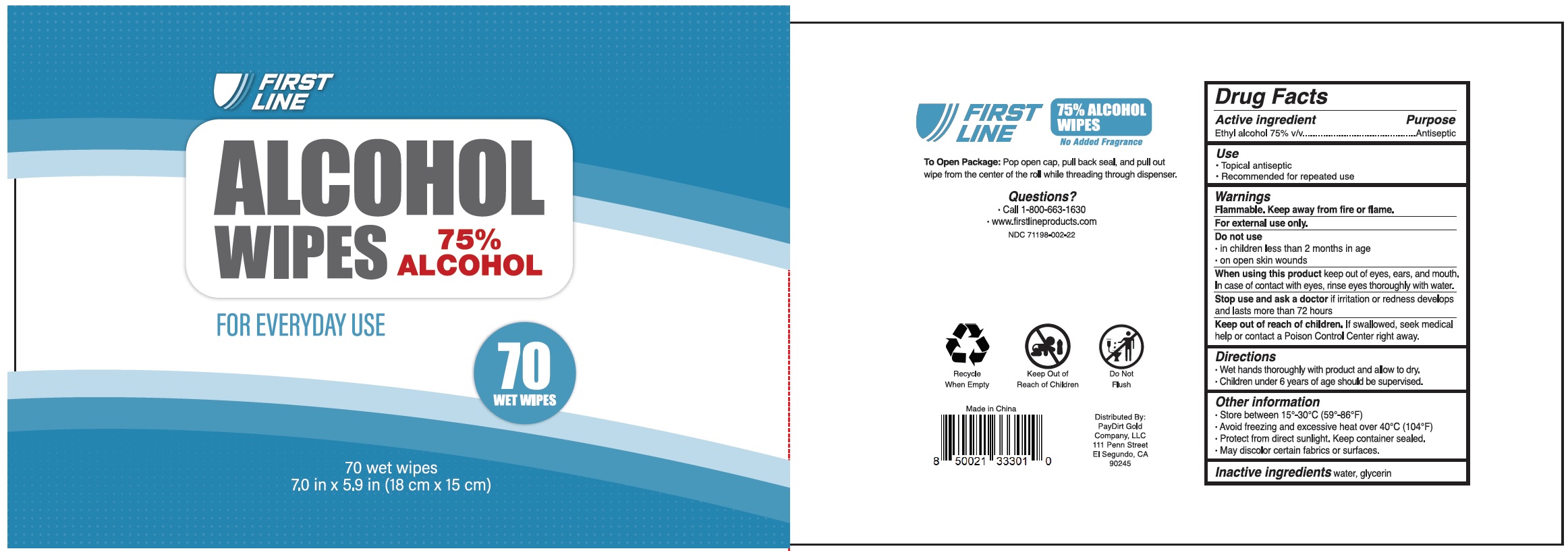 DRUG LABEL: First Line Alcohol Wipes
NDC: 81043-001 | Form: CLOTH
Manufacturer: PayDirt Gold Company, LLC
Category: otc | Type: HUMAN OTC DRUG LABEL
Date: 20201112

ACTIVE INGREDIENTS: ALCOHOL 0.75 mL/1 mL
INACTIVE INGREDIENTS: WATER; GLYCERIN

First Line Alcohol Wipes

Active ingredient

Ethyl alcohol 75% v/v

Purpose

Antiseptic

Use

- Topical antiseptic
- Recommended for repeated use

Warnings

Flammable. Keep away from fire or flame.

For external use only.

Do not use

- in children less than 2 months in age
- on open skin wounds

When using this product

keep out of eyes, ears, and mouth. In case of contact with eyes, rinse eyes thoroughly with water.

Stop use and ask a doctor

if irritation or redness develops and lasts more than 72 hours

Keep out of reach of children.

If swallowed, seek medical help or contact a Poison Control Center right away.

Directions

- Wet hands thoroughly with product and allow to dry.
- Children under 6 years of age should be supervised.

Other information

- Store between 15°-30°C (59°-86°F)
- Avoid freezing and excessive heat over 40°C (104°F)
- Protect from direct sunlight. Keep container sealed.
- May discolor certain fabrics or surfaces.

Inactive ingredients

water, glycerin